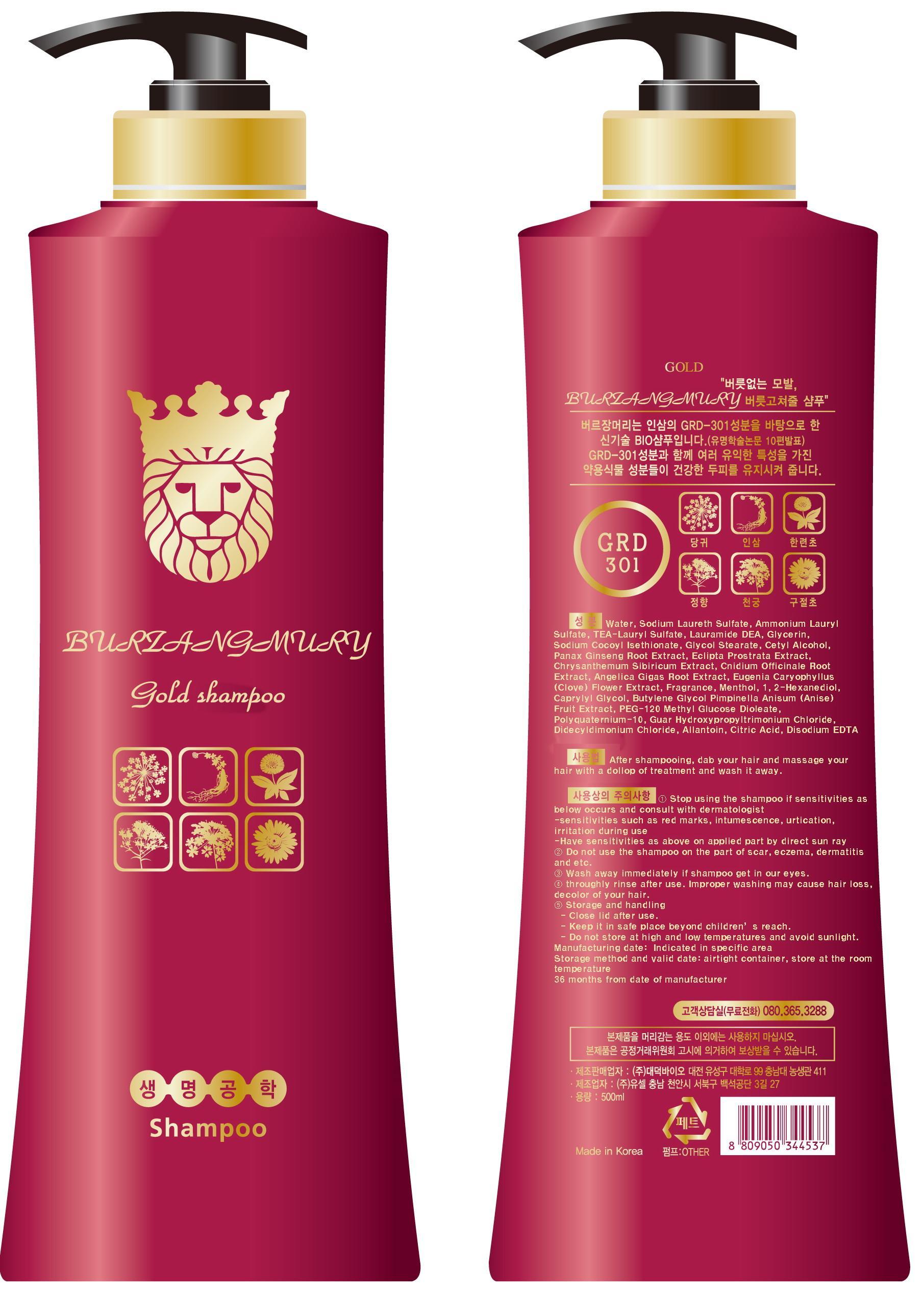 DRUG LABEL: BURZANGMURY GOLD
NDC: 58906-1001 | Form: SHAMPOO
Manufacturer: Dae Deok bio Inc 
Category: otc | Type: HUMAN OTC DRUG LABEL
Date: 20130816

ACTIVE INGREDIENTS: GLYCERIN 0.01 g/1 mL
INACTIVE INGREDIENTS: WATER; SODIUM LAURETH SULFATE; AMMONIUM LAURYL SULFATE; LAURIC DIETHANOLAMIDE

Drug Facts

ACTIVE INGREDIENT

glycerin

INACTIVE INGREDIENT

water,Sodium Laureth Sulfate, ammonium lauryl sulfate,TEA-Lauryl Sulfate, Lauramide DEA, glycerin, Sodium Cocoyl Isethionate, Glycol Stearate, cetyl alcohol, ginseng extract, eclipta prostrata extract, siberian chrysanthemum extract, cnidium rhizome extract, Korean angelica root extract, clove flower extract, perfume, menthol, 1,2-hexandiol, Caprylyl Glycol, butylene glycol, aniseed extract, PEG-120 Methyl Glucose Dioleate, polyquaternium-10, Guar Hydroxypropyltrimonium Chloride, Dicetyldimonium Chloride, allantoin, citric acid, Disodium EDTA

PURPOSE

hair growth, loss prevention

keep out of reach of the children

INDICATIONS AND USAGE

After throughly wetting the hair and scalp with water and putting a dollop of shampoo on the hair, massage your scalp for 2~3 minutes with foam and rinse away the shampoo. A person who have problem with hair or a person with long hair can have more effect by shampooing one more time

WARNINGS

- Stop using the shampoo if sensitivities as below occurs and consult with dermatologist
- sensitivities such as red marks, intumescence, urtication, irritation during use
-Have sensitivities as above on applied part by direct sun ray
- Do not use the shampoo on the part of scar, eczema, dermatitis and etc.
- Wash away immediately if shampoo get in our eyes.
- throughly rinse after use. Improper washing may cause hair loss, decolor of your hair.
- Storage and handling
- Close lid after use.
- Keep it in safe place beyond children¡¯s reach.
- Do not store at high and low temperatures and avoid sunlight.

DOSAGE AND ADMINISTRATION

for external use only